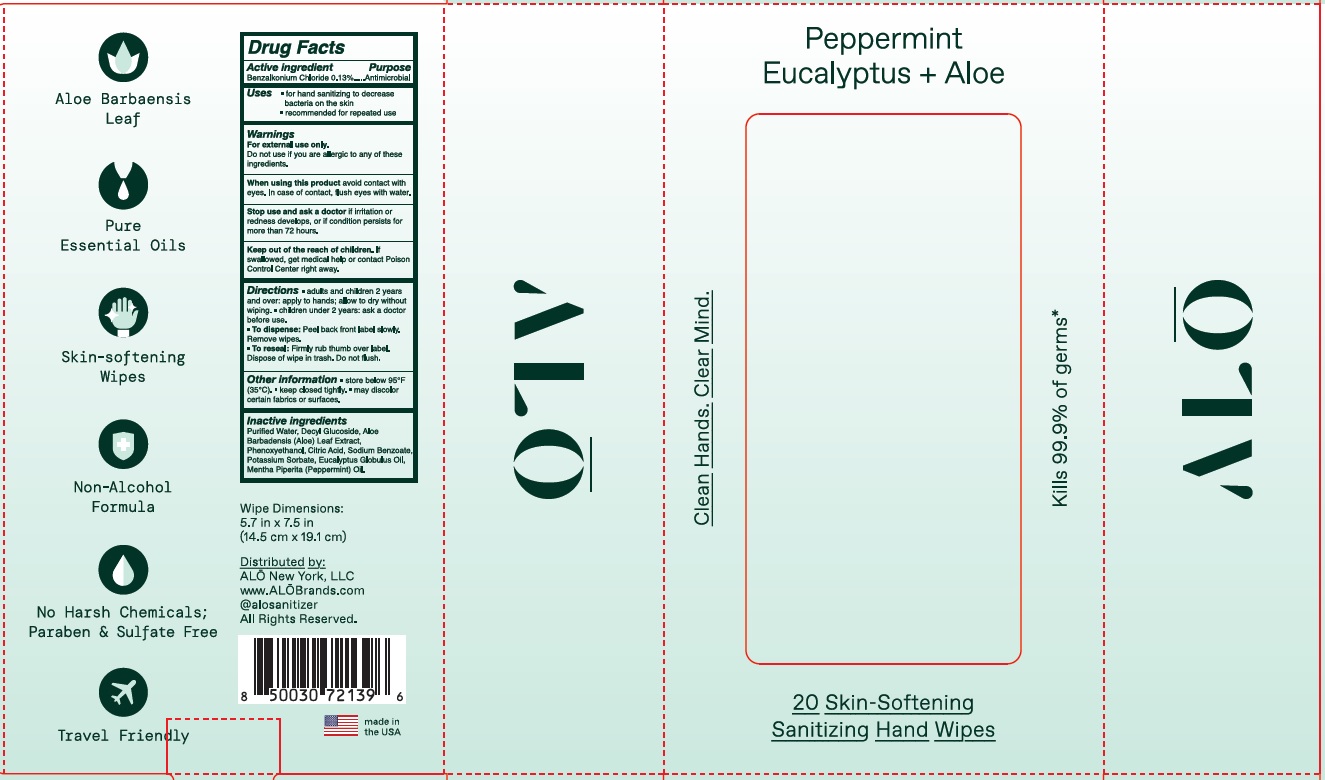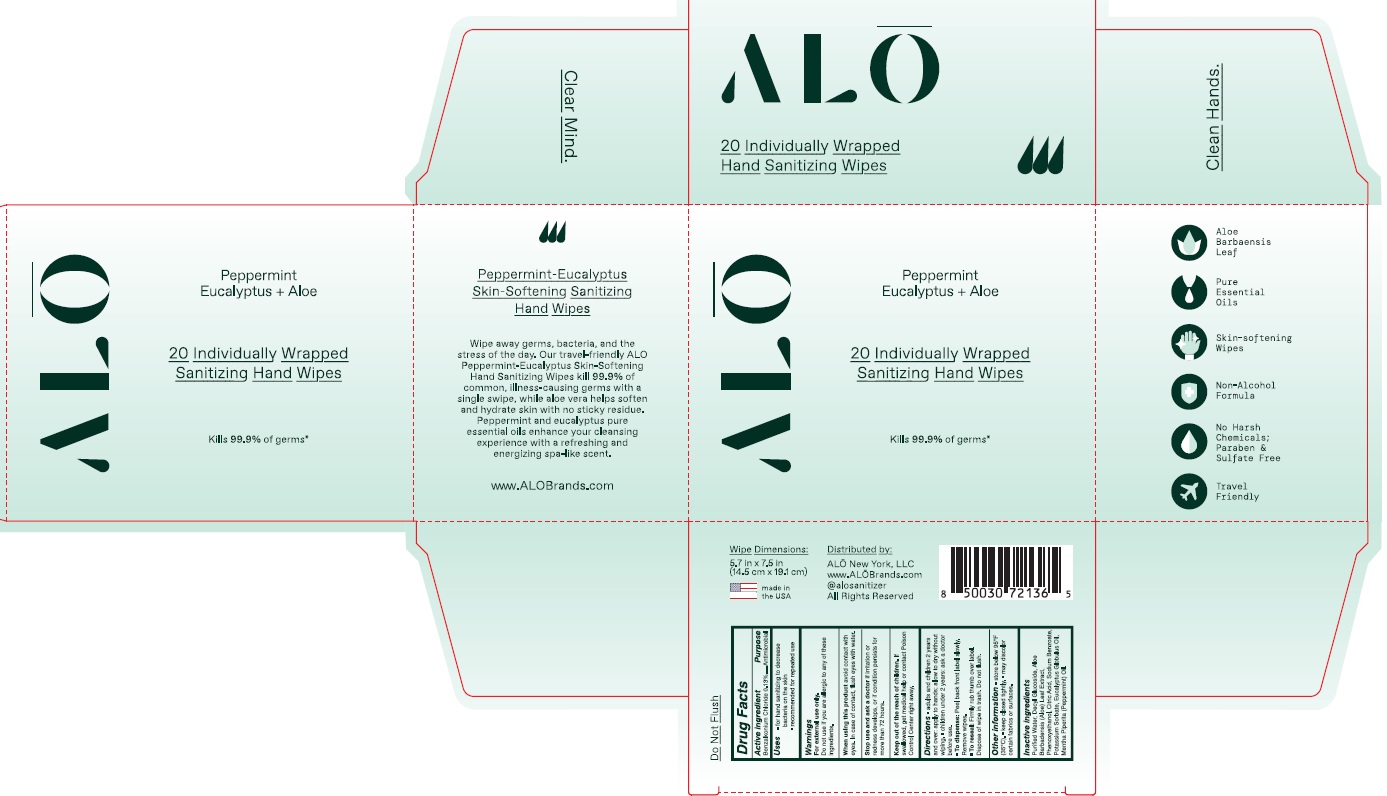 DRUG LABEL: Benzalkonium Chloride
NDC: 82355-550 | Form: CLOTH
Manufacturer: ALO NEW YORK LLC
Category: otc | Type: HUMAN OTC DRUG LABEL
Date: 20260115

ACTIVE INGREDIENTS: BENZALKONIUM CHLORIDE 0.0013 mg/100 mg
INACTIVE INGREDIENTS: WATER; ALOE VERA LEAF; PHENOXYETHANOL; MENTHA PIPERITA; SODIUM BENZOATE; DECYL GLUCOSIDE; EUCALYPTUS GLOBULUS WHOLE; CITRIC ACID MONOHYDRATE; POTASSIUM SORBATE

Peppermint Eucalyptus + Aloe

Active ingredients

Benzalkonium Chloride 0.13%

Purpose

Antimicrobial

Uses

- for hand sanitizing to decrease bacteria on the skin
- recommended for repeated use

Warnings

For external use only.

Do not use

if you are allergic to any of these ingredients.

When using this product

avoid contact with eyes. In case of contact, flush eyes with water.

Stop use and ask a doctor

if irritation or redness develops, or if condition persists for more than 72 hours.

Keep out of the reach of children.

If swallowed, get medical help or contact Poison Control Center right away.

Directions

- adults and children 2 years and over: apply to hands: allow to dry without wiping
- children under 2 years: ask a doctor before use.
- To dispense: Peel back fron label slowly. Remove wipes.
- To reseal: Firmly rub thumb over label. Dispose of wipe in trash. Do not flush.

Other information

store below 95

- store below 95°F (35°C).
- keep closed tightly
- may discolor certain fabrics or surfaces.

Inactive ingredients

Purified Water, Decyl Glucoside, Aloe Barbadensis (Aloe) Leaf Extract, Phenoxyethanol, Citric Acid, Sodium Benzoate, Potassium Sorbate, Eucalyptus Globulus Oil, Mentha Piperita (Peppermint) Oil.

Principal Display Panel

ALO

20 Skin-Softening Sanitizing Hand Wipes

ALO

20 Individually Wrapped Sanitizing Hand Wipes